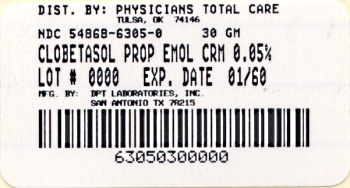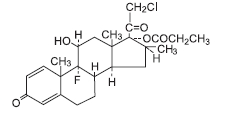 DRUG LABEL: Clobetasol Propionate
NDC: 54868-6305 | Form: EMULSION
Manufacturer: Physicians Total Care, Inc.
Category: prescription | Type: HUMAN PRESCRIPTION DRUG LABEL
Date: 20100604

ACTIVE INGREDIENTS: CLOBETASOL PROPIONATE 0.5 mg/1 g
INACTIVE INGREDIENTS: CETETH-20; CETOSTEARYL ALCOHOL; ANHYDROUS CITRIC ACID; DIMETHICONE 350; IMIDUREA; ISOPROPYL MYRISTATE; PROPYLENE GLYCOL; WATER; SODIUM CITRATE

Clobetasol Propionate Cream-Emollient, 0.05%

Rx only

FOR TOPICAL DERMATOLOGIC USE ONLY - NOT FOR OPHTHALMIC, ORAL, OR INTRAVAGINAL USE.

DESCRIPTION

Clobetasol Propionate Cream-Emollient, 0.05% contains the active compound clobetasol propionate, a synthetic corticosteroid, for topical dermatologic use. Clobetasol, an analog of prednisolone, has a high degree of glucocorticoid activity and a slight degree of mineralocorticoid activity.

Chemically, clobetasol propionate is (11ß,16ß)-21- chloro-9-fluoro-11-hydroxy-16-methyl-17-(1-oxopropoxy)- pregna-1,4-diene-3,20-dione, and it has the following structural formula:

Clobetasol propionate has the molecular formula C25H32CIFO5 and a molecular weight of 467. It is a white to cream-colored crystalline powder insoluble in water.

Clobetasol propionate cream-emollient contains clobetasol propionate 0.5 mg/g in an emollient base of cetomacrogol 1000, cetostearyl alcohol, citric acid, dimethicone 360, imidurea as a preservative, isopropyl myristate, propylene glycol, purified water, and sodium citrate.

CLINICAL PHARMACOLOGY

Like other topical corticosteroids, clobetasol propionate has antiinflammatory, antipruritic, and vasoconstrictive properties. The mechanism of the anti-inflammatory activity of the topical steroids, in general, is unclear. However, corticosteroids are thought to act by the induction of phospholipase A2 inhibitory proteins, collectively called lipocortins. It is postulated that these proteins control the biosynthesis of potent mediators of inflammation such as prostaglandins and leukotrienes by inhibiting the release of their common precursor, arachidonic acid. Arachidonic acid is released from membrane phospholipids by phospholipase A2.

Pharmacokinetics

The extent of percutaneous absorption of topical corticosteroids is determined by many factors, including the vehicle and integrity of the epidermal barrier. Occlusive dressing with hydrocortisone for up to 24 hours has not been demonstrated to increase penetration; however, occlusion of hydrocortisone for 96 hours markedly enhances penetration. Topical corticosteroids can be absorbed from normal intact skin. Inflammation and/or other disease processes in the skin may increase percutaneous absorption.

Studies performed with clobetasol propionate cream-emollient indicate that it is in the super-high range of potency as compared with other topical corticosteroids.

INDICATIONS AND USAGE

Clobetasol propionate cream-emollient is a super-high potency corticosteroid formulation indicated for the relief of the inflammatory and pruritic manifestations of corticosteroid-responsive dermatoses. Treatment beyond 2 consecutive weeks is not recommended, and the total dosage should not exceed 50 g/week because of the potential for the drug to suppress the hypothalamic-pituitary- adrenal (HPA) axis. Use in pediatric patients under 12 years of age is not recommended.

In the treatment of moderate to severe plaque-type psoriasis, clobetasol propionate cream-emollient applied to 5% to 10% of body surface area can be used up to 4 consecutive weeks. The total dosage should not exceed 50 g/week. When dosing for more than 2 weeks, any additional benefits of extending treatment should be weighed against the risk of HPA suppression. Treatment beyond 4 consecutive weeks is not recommended. Patients should be instructed to use clobetasol propionate cream-emollient for the minimum amount of time necessary to achieve the desired results (see PRECAUTIONS and INDICATIONS AND USAGE). Use in pediatric patients under 16 years of age has not been studied.

CONTRAINDICATIONS

Clobetasol Propionate Cream-Emollient, 0.05% is contraindicated in those patients with a history of hypersensitivity to any of the components of the preparation.

PRECAUTIONS

General

Clobetasol propionate is a highly potent topical corticosteroid that has been shown to suppress the HPA axis at doses as low as 2 g/day.

Systemic absorption of topical corticosteroids can produce reversible HPA axis suppression with the potential for glucocorticosteroid insufficiency after withdrawal from treatment. Manifestations of Cushing syndrome, hyperglycemia, and glucosuria can also be produced in some patients by systemic absorption of topical corticosteroids while on therapy.

Patients applying a topical steroid to a large surface area or to areas under occlusion should be evaluated periodically for evidence of HPA axis suppression. This may be done by using the ACTH stimulation, A.M. plasma cortisol, and urinary free cortisol tests. Patients receiving super-potent corticosteroids should not be treated for more than 2 weeks at a time, and only small areas should be treated at any one time due to the increased risk of HPA suppression.

In a controlled clinical trial involving patients with moderate to severe plaque-type psoriasis, clobetasol propionate cream-emollient applied to 5% to 10% of body surface area resulted in additional benefits in the treatment of patients for 4 consecutive weeks. In this trial, there were no clobetasol-treated patients with clinically significant decreases in morning cortisol levels after 4 weeks of treatment; however, morning cortisol levels may not identify patients with adrenal dysfunction. Therefore, the additional benefits of extending treatment beyond 2 weeks should be weighed against the potential for HPA suppression. Therapy should be discontinued when control has been achieved. Treatment beyond 4 consecutive weeks is not recommended.

If HPA axis suppression is noted, an attempt should be made to withdraw the drug, to reduce the frequency of application, or to substitute a less potent corticosteroid. Recovery of HPA axis function is generally prompt upon discontinuation of topical corticosteroids. Infrequently, signs and symptoms of glucocorticosteroid insufficiency may occur that require supplemental systemic corticosteroids. For information on systemic supplementation, see prescribing information for those products.

Pediatric patients may be more susceptible to systemic toxicity from equivalent doses due to their larger skin surface to body mass ratios (see PRECAUTIONS: Pediatric Use). The use of clobetasol propionate cream-emollient for 4 consecutive weeks has not been studied in pediatric patients under 16 years of age.

Clobetasol propionate cream-emollient contains the excipient imidurea which releases traces of formaldehyde as a breakdown product. Formaldehyde may cause allergic sensitization or irritation upon contact with the skin.

If irritation develops, clobetasol propionate cream-emollient should be discontinued and appropriate therapy instituted. Allergic contact dermatitis with corticosteroids is usually diagnosed by observing a failure to heal rather than noting a clinical exacerbation as with most topical products not containing corticosteroids. Such an observation should be corroborated with appropriate diagnostic patch testing.

If concomitant skin infections are present or develop, an appropriate antifungal or antibacterial agent should be used. If a favorable response does not occur promptly, use of clobetasol propionate cream-emollient should be discontinued until the infection has been adequately controlled.

Clobetasol propionate cream-emollient should not be used in the treatment of rosacea or perioral dermatitis, and should not be used on the face, groin, or axillae.

Information for Patients

Patients using topical corticosteroids should receive the following information and instructions:

1. This medication is to be used as directed by the physician. It is for external use only. Avoid contact with the eyes.
2. This medication should not be used for any disorder other than that for which it was prescribed.
3. The treated skin area should not be bandaged, otherwise covered, or wrapped so as to be occlusive unless directed by the physician.
4. Patients should report any signs of local adverse reactions to the physician.
5. Patients should inform their physicians that they are using clobetasol propionate cream-emollient if surgery is contemplated.
6. This medication should not be used on the face, underarms, or groin areas.
7. As with other corticosteroids, therapy should be discontinued when control has been achieved. If no improvement is seen within 2 weeks, contact the physician.

Laboratory Tests

The following tests may be helpful in evaluating patients for HPA axis suppression:

ACTH stimulation test
A.M. plasma cortisol test
Urinary free cortisol test

Carcinogenesis, Mutagenesis, Impairment of Fertility

Long-term animal studies have not been performed to evaluate the carcinogenic potential of clobetasol propionate.

Studies in the rat following subcutaneous administration at dosage levels up to 50 mcg/kg/day revealed that the females exhibited an increase in the number of resorbed embryos and a decrease in the number of living fetuses at the highest dose.

Clobetasol propionate was nonmutagenic in 3 different test systems: the Ames test, the Saccharomyces cerevisiae gene conversion assay, and the E. coli B WP2 fluctuation test.

Pregnancy

Teratogenic Effects

Pregnancy Category C

Corticosteroids have been shown to be teratogenic in laboratory animals when administered systemically at relatively low dosage levels. Some corticosteroids have been shown to be teratogenic after dermal application to laboratory animals.

Clobetasol propionate has not been tested for teratogenicity when applied topically; however, it is absorbed percutaneously, and when administered subcutaneously it was a significant teratogen in both the rabbit and mouse. Clobetasol propionate has greater teratogenic potential than steroids that are less potent.

Teratogenicity studies in mice using the subcutaneous route resulted in fetotoxicity at the highest dose tested (1 mg/kg) and teratogenicity at all dose levels tested down to 0.03 mg/kg. These doses are approximately 1.4 and 0.04 times, respectively, the human topical dose of clobetasol propionate cream-emollient. Abnormalities seen included cleft palate and skeletal abnormalities.

In rabbits, clobetasol propionate was teratogenic at doses of 3 and 10 mcg/kg. These doses are approximately 0.02 and 0.05 times, respectively, the human topical dose of clobetasol propionate cream-emollient. Abnormalities seen included cleft palate, cranioschisis, and other skeletal abnormalities.

There are no adequate and well-controlled studies of the teratogenic potential of clobetasol propionate in pregnant women. Clobetasol propionate cream-emollient should be used during pregnancy only if the potential benefit justifies the potential risk to the fetus.

Nursing Mothers

Systemically administered corticosteroids appear in human milk and could suppress growth, interfere with endogenous corticosteroid production, or cause other untoward effects. It is not known whether topical administration of corticosteroids could result in sufficient systemic absorption to produce detectable quantities in human milk. Because many drugs are excreted in human milk, caution should be exercised when clobetasol propionate cream-emollient is administered to a nursing woman.

Pediatric Use

Safety and effectiveness of clobetasol propionate cream-emollient in pediatric patients have not been established. Use in pediatric patients under 12 years of age is not recommended. For continued use beyond 2 consecutive weeks, the safety of clobetasol propionate cream-emollient has not been studied. Because of a higher ratio of skin surface area to body mass, pediatric patients are at a greater risk than adults of HPA axis suppression and Cushing syndrome when they are treated with topical corticosteroids. They are therefore also at greater risk of adrenal insufficiency during or after withdrawal of treatment. Adverse effects including striae have been reported with inappropriate use of topical corticosteroids in infants and children.

HPA axis suppression, Cushing syndrome, linear growth retardation, delayed weight gain, and intracranial hypertension have been reported in children receiving topical corticosteroids. Manifestations of adrenal suppression in children include low plasma cortisol levels and absence of response to ACTH stimulation. Manifestations of intracranial hypertension include bulging fontanelles, headaches, and bilateral papilledema.

Geriatric Use

A limited number of patients at or above 65 years of age (n = 34) have been treated with clobetasol propionate cream-emollient in US clinical trials. While the number of patients is too small to permit separate analysis of efficacy and safety, the single adverse reaction reported in this population was similar to those reactions reported by younger patients. Based on available data, no adjustment of dosage of clobetasol propionate cream-emollient in geriatric patients is warranted.

ADVERSE REACTIONS

In controlled trials with all clobetasol propionate formulations, the following adverse reactions have been reported: burning/stinging, pruritus, irritation, erythema, folliculitis, cracking and fissuring of the skin, numbness of the fingers, tenderness in the elbow, skin atrophy, and telangiectasia. The incidence of local adverse reactions reported in the trials with clobetasol propionate cream-emollient was <2% of patients treated with the exception of burning/stinging, which occurred in 5% of treated patients.

Cushing syndrome has been reported in infants and adults as a result of prolonged use of other topical clobetasol propionate formulations.

The following additional local adverse reactions are reported infrequently with topical corticosteroids, but may occur more frequently with super-high potency corticosteroids such as clobetasol propionate cream-emollient. These reactions are listed in an approximately decreasing order of occurrence: dryness, hypertrichosis, acneiform eruptions, hypopigmentation, perioral dermatitis, allergic contact dermatitis, secondary infection, striae, and miliaria.

To report SUSPECTED ADVERSE REACTIONS, contact Hi-Tech Pharmacal Co., Inc. at 1-800-262-9010 or FDA at 1-800-FDA-1088 or www.fda.gov/medwatch.

OVERDOSAGE

Topically applied Clobetasol Propionate Cream-Emollient, 0.05% can be absorbed in sufficient amounts to produce systemic effects (see PRECAUTIONS).

DOSAGE AND ADMINISTRATION

Apply a thin layer of clobetasol propionate cream-emollient, 0.05% to the affected skin areas twice daily and rub in gently and completely (see INDICATIONS AND USAGE).

Clobetasol propionate cream-emollient is a super-high potency topical corticosteroid; therefore, treatment should be limited to 2 consecutive weeks and amounts greater than 50 g/week should not be used.

In moderate to severe plaque-type psoriasis, clobetasol propionate cream-emollient applied to 5% to 10% of body surface area can be used up to 4 weeks. The total dosage should not exceed 50 g/week. When dosing for more than 2 weeks, any additional benefits of extending treatment should be weighed against the risk of HPA suppression. As with other highly active corticosteroids, therapy should be discontinued when control has been achieved. If no improvement is seen within 2 weeks, reassessment of diagnosis may be necessary. Treatment beyond 4 consecutive weeks is not recommended. Use in pediatric patients under 16 years of age has not been studied.

Clobetasol propionate cream-emollient should not be used with occlusive dressings.

Geriatric Use

In studies where geriatric patients (65 years of age or older, see PRECAUTIONS) have been treated with clobetasol propionate cream-emollient, safety did not differ from that in younger patients; therefore, no dosage adjustment is recommended.

HOW SUPPLIED

Clobetasol Propionate Cream-Emollient, 0.05% is supplied in 30-g tubes (NDC 54868-6305-0).

Store between 15° and 30° C (59° and 86° F).

Clobetasol propionate cream-emollient should not be refrigerated.

Rx Only

Distributed by:

Hi-Tech Pharmacal Co., Inc.

Amityville, NY 11701

Manufactured by:

DPT Laboratories Ltd

San Antonio, TX 78215

Rev. 270:00 10/09

129160-1009

Additional barcode labeling by:
Physicians Total Care, Inc.
Tulsa, OK 74146

PACKAGE/LABEL PRINCIPAL DISPLAY PANEL

NDC 54868-6305-0

Clobetasol Propionate Cream-Emollient, 0.05%

30 grams

For dermatologic use only.

Not for ophthalmic use.

Rx only